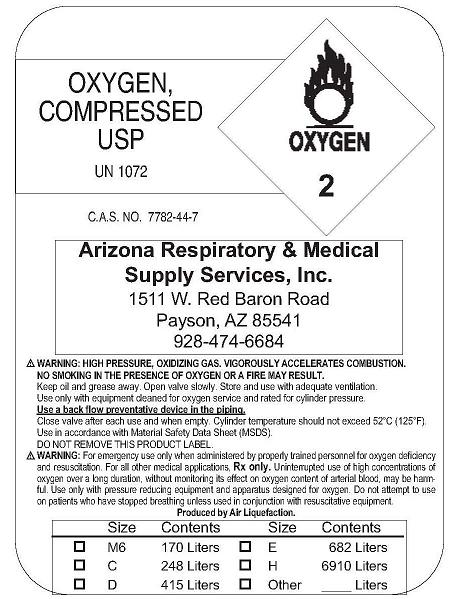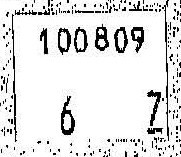 DRUG LABEL: Oxygen
NDC: 63218-4000 | Form: GAS
Manufacturer: Arizona Respiratory & Medical Supply Services, Inc.
Category: prescription | Type: HUMAN PRESCRIPTION DRUG LABEL
Date: 20091111

ACTIVE INGREDIENTS: Oxygen 99 L/100 L

Oxygen